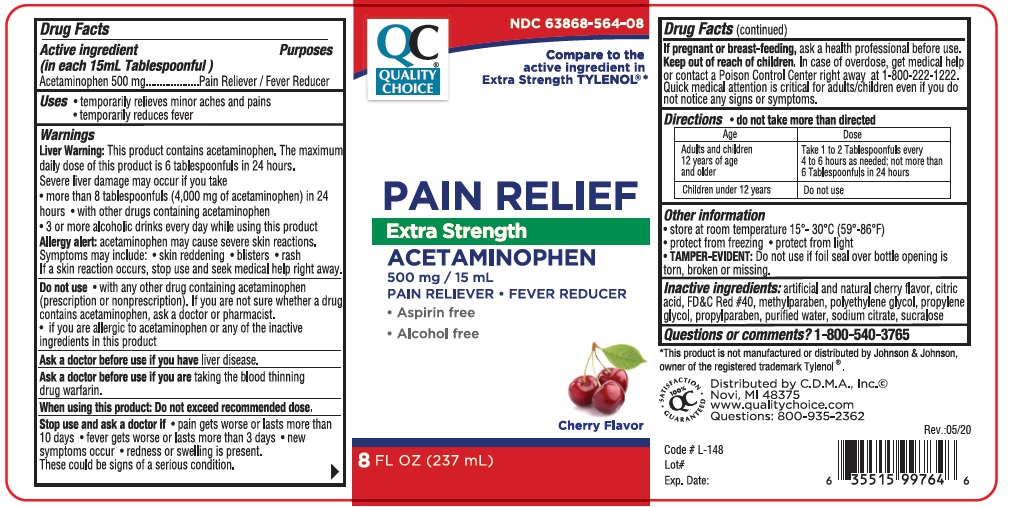 DRUG LABEL: Qaulity Choice Pain Relief Extra Strength
NDC: 63868-564 | Form: LIQUID
Manufacturer: CHAIN DRUG MARKETING ASSOCIATION INC
Category: otc | Type: HUMAN OTC DRUG LABEL
Date: 20201223

ACTIVE INGREDIENTS: ACETAMINOPHEN 500 mg/15 mL
INACTIVE INGREDIENTS: ANHYDROUS CITRIC ACID; FD&C RED NO. 40; METHYLPARABEN; POLYETHYLENE GLYCOL, UNSPECIFIED; PROPYLENE GLYCOL; PROPYLPARABEN; WATER; SODIUM CITRATE; SUCRALOSE

Active Ingredient

Acetaminophen 500 mg

Purpose

Pain Reliever/Fever Reducer

Uses

- temporarily relieves minor aches and pains

- temporarily reduces fever

Warnings

Liver warning: This product contains acetaminophen. The maximum daily dose of this product is 6 tablespoonfuls in 24 hours. Sever liver damage may occur if you take

- more than 8 tablespoonfuls (4,000 mg of acetaminophen) in 24 hours
- with other drugs containing acetaminophen
- 3 or more alcoholic drinks everyd ay while using this product

Allergy alert: acetaminophen may cause sever skin reactions. Symptoms may include:

- skin reddening
- blisters
- rash
- If a skin reaction occurs, stop use and seek mdical help right away.

Do not use with any other drug containing acetaminophen (prescription or nonprescription). If you are not sure whether a drug contains acetaminophen, ask a doctor or pharmacist.

If you are allergic to acetaminophen or any of the inactive ingredients in thris product.
Ask a doctor before use if you have liver disease
Ask a doctor before use if you are taking the blodd thinning drug warfarin.
When using this product: Do not exceed recomended dose.
Stop use and ask a doctor if:

- pain gets worse or lasts more than 10 days
- fever gets worse or lasts more than 3 days
- new symptoms occur
- redness or swelling is present

These could be signs of a serious condition.

PREGNANCY OR BREAST FEEDING

If pregnant or breast feeding, ask a health professional before use.

Keep out of reach of children. In case of overdose, get midcal help or contact a Poison Control Center right away at 1-800-222-1222. Quick medical attention is critical for adults/children even if you do not notice any signs or symptoms.

DOSAGE AND ADMINISTRATION

Directions Do not take more than directed

Age | Dose
Adults and children12 years of age and older | Take 1 to 2 tablespoonfuls every 4 to 6 hours as needed. not more than 6 tablespoonfuls in 24 hours
Children under 12 years | Do not use

INACTIVE INGREDIENT

Inactive ingredients: artificial and natural cherry flavor, citric acid, FD&C Red #40, methylparaben, polyethylene glycol, propylene glycol, porpylparaben, purified water, sodium citrate, sucralose.

QUESTIONS

Question or comments? 1-800-540-3765